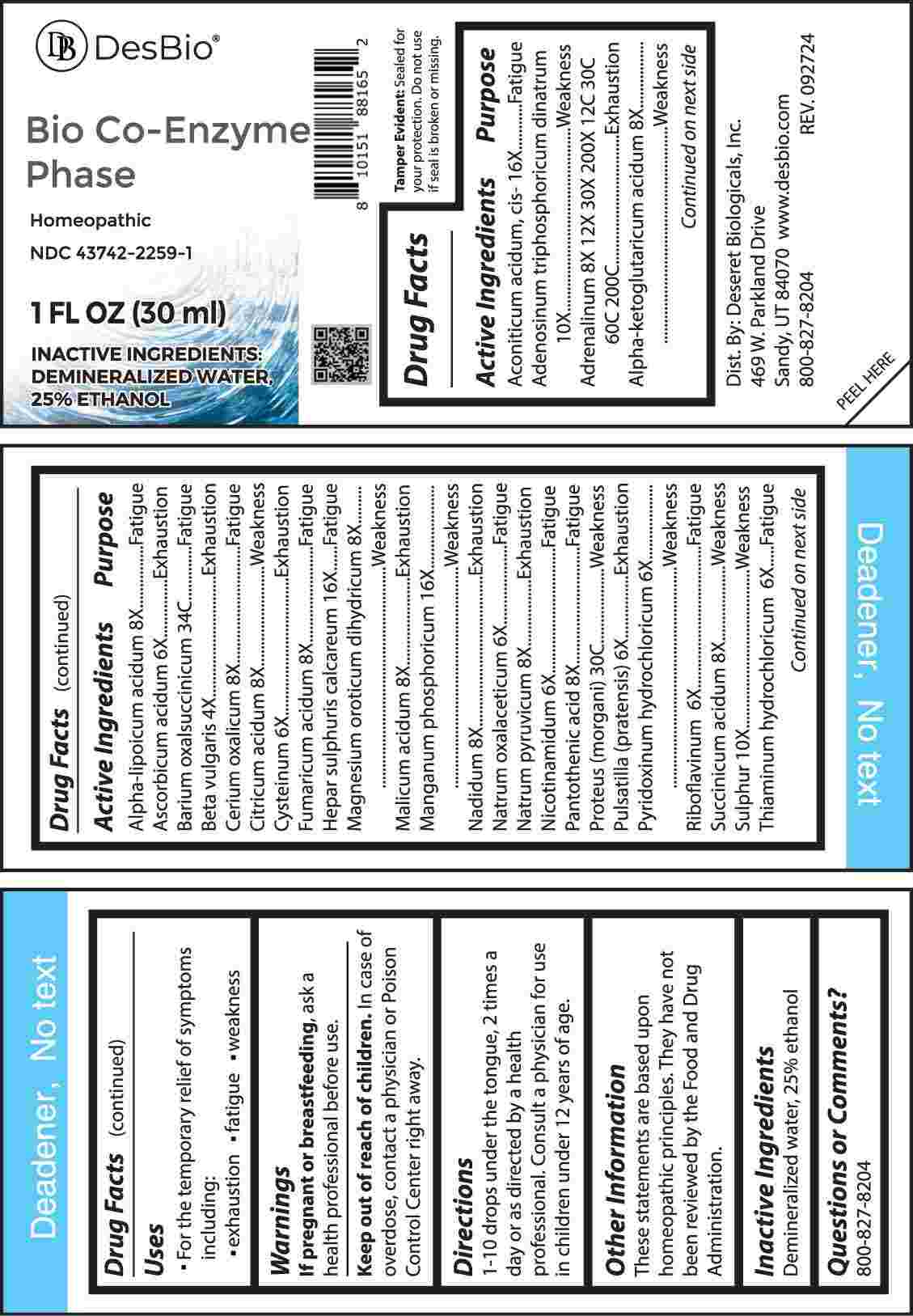 DRUG LABEL: Bio Co Enzyme Phase
NDC: 43742-2259 | Form: LIQUID
Manufacturer: Deseret Biologicals, Inc.
Category: homeopathic | Type: HUMAN OTC DRUG LABEL
Date: 20250408

ACTIVE INGREDIENTS: ACONITIC ACID 16 [hp_X]/1 mL; ADENOSINE TRIPHOSPHATE DISODIUM 10 [hp_X]/1 mL; EPINEPHRINE 8 [hp_X]/1 mL; OXOGLURIC ACID 8 [hp_X]/1 mL; ALPHA LIPOIC ACID 8 [hp_X]/1 mL; ASCORBIC ACID 6 [hp_X]/1 mL; BARIUM OXALOSUCCINATE 34 [hp_C]/1 mL; BETA VULGARIS WHOLE 4 [hp_X]/1 mL; CEROUS OXALATE NONAHYDRATE 8 [hp_X]/1 mL; ANHYDROUS CITRIC ACID 8 [hp_X]/1 mL; CYSTEINE 6 [hp_X]/1 mL; FUMARIC ACID 8 [hp_X]/1 mL; CALCIUM SULFIDE 16 [hp_X]/1 mL; MAGNESIUM OROTATE DIHYDRATE 8 [hp_X]/1 mL; MALIC ACID 8 [hp_X]/1 mL; MANGANESE PHOSPHATE, DIBASIC 16 [hp_X]/1 mL; NADIDE 8 [hp_X]/1 mL; SODIUM DIETHYL OXALACETATE 6 [hp_X]/1 mL; SODIUM PYRUVATE 8 [hp_X]/1 mL; NIACINAMIDE 6 [hp_X]/1 mL; PANTOTHENIC ACID 8 [hp_X]/1 mL; PROTEUS MORGANII 30 [hp_C]/1 mL; PULSATILLA PRATENSIS WHOLE 6 [hp_X]/1 mL; PYRIDOXINE HYDROCHLORIDE 6 [hp_X]/1 mL; RIBOFLAVIN 6 [hp_X]/1 mL; SUCCINIC ACID 8 [hp_X]/1 mL; SULFUR 10 [hp_X]/1 mL; THIAMINE HYDROCHLORIDE 6 [hp_X]/1 mL
INACTIVE INGREDIENTS: WATER; ALCOHOL

DRUG FACTS:

ACTIVE INGREDIENTS:

Aconiticum Acidum 16X, Cis-, Adenosinum Triphosphoricum Dinatrum 10X, Adrenalinum 8X, 12X, 30X, 200X, 12C, 30C, 60C, 200C, Alpha-Ketoglutaricum Acidum 8X, Alpha-Lipoicum Acidum 8X, Ascorbicum Acidum 6X, Barium Oxalsuccinicum 34C, Beta Vulgaris 4X, Cerium Oxalicum 8X, Citricum Acidum 8X, Cysteinum 6X, Fumaricum Acidum 8X, Hepar Sulphuris Calcareum 16X, Magnesium Oroticum Dihydricum 8X, Malicum Acidum 8X, Manganum Phosphoricum 16X, Nadidum 8X, Natrum Oxalaceticum 6X, Natrum Pyruvicum 8X, Nicotinamidum 6X, Pantothenic Acid 8X, Proteus (Morgani) 30C, Pulsatilla (Pratensis) 6X, Pyridoxinum Hydrochloricum 6X, Riboflavinum 6X, Succinicum Acidum 8X, Sulphur 10X, Thiaminum Hydrochloricum 6X.

PURPOSE:

Aconiticum Acidum, Cis - Fatigue, Adenosinum Triphosphoricum Dinatrum - Weakness, Adrenalinum - Exhaustion, Alpha-Ketoglutaricum Acidum - Weakness, Alpha-Lipoicum Acidum - Fatigue, Ascorbicum Acidum - Exhaustion, Barium Oxalsuccinicum - Fatigue, Beta Vulgaris - Exhaustion, Cerium Oxalicum - Fatigue, Citricum Acidum - Weakness, Cysteinum - Exhaustion, Fumaricum Acidum - Fatigue, Hepar Sulphuris Calcareum - Fatigue, Magnesium Oroticum Dihydricum - Weakness, Malicum Acidum - Exhaustion, Manganum Phosphoricum - Weakness, Nadidum - Exhaustion, Natrum Oxalaceticum - Fatigue, Natrum Pyruvicum - Exhaustion, Nicotinamidum - Fatigue, Pantothenic Acid - Fatigue, Proteus (Morgani) - Weakness, Pulsatilla (Pratensis) – Exhaustion, Pyridoxinum Hydrochloricum - Weakness, Riboflavinum - Fatigue, Succinicum Acidum - Weakness, Sulphur - Weakness, Thiaminum Hydrochloricum - Fatigue

USES:

• For the temporary relief of symptoms including:

• exhaustion • fatigue • weakness

These statements are based upon homeopathic principles. They have not been reviewed by the Food and Drug Administration.

WARNINGS:

If pregnant or breastfeeding, ask a health professional before use.

Keep out of reach of children. In case of overdose, contact a physician or Poison Control Center right away.

Tamper Evident: Sealed for your protection. Do not use if seal is broken or missing.

KEEP OUT OF REACH OF CHILDREN:

In case of overdose, contact a physician or Poison Control Center right away.

DIRECTIONS:

1-10 drops under the tongue, 2 times a day or as directed by a health professional. Consult a physician for use in children under 12 years of age.

INACTIVE INGREDIENTS:

Demineralized water, 25% ethanol

QUESTIONS:

Dist. By: Deseret Biologicals, Inc.

469 W. Parkland Drive

Sandy, UT 84070

www.desbio.com

800-827-8204

PACKAGE LABEL DISPLAY:

DesBio

Bio Co-Enzyme Phase

Homeopathic
NDC 43742-2259-1
1 FL OZ (30 ml)